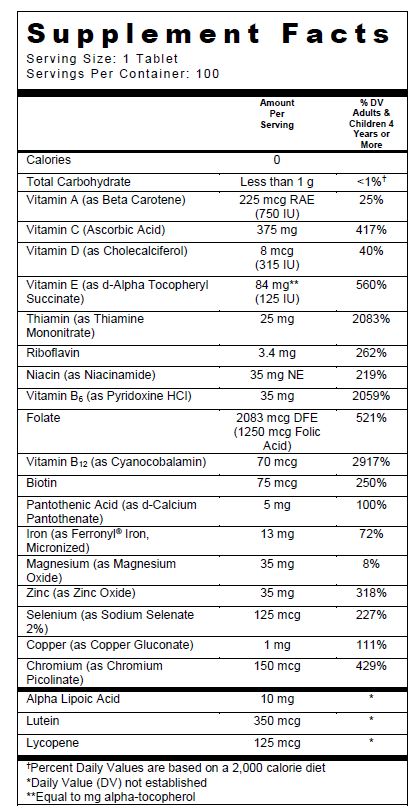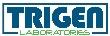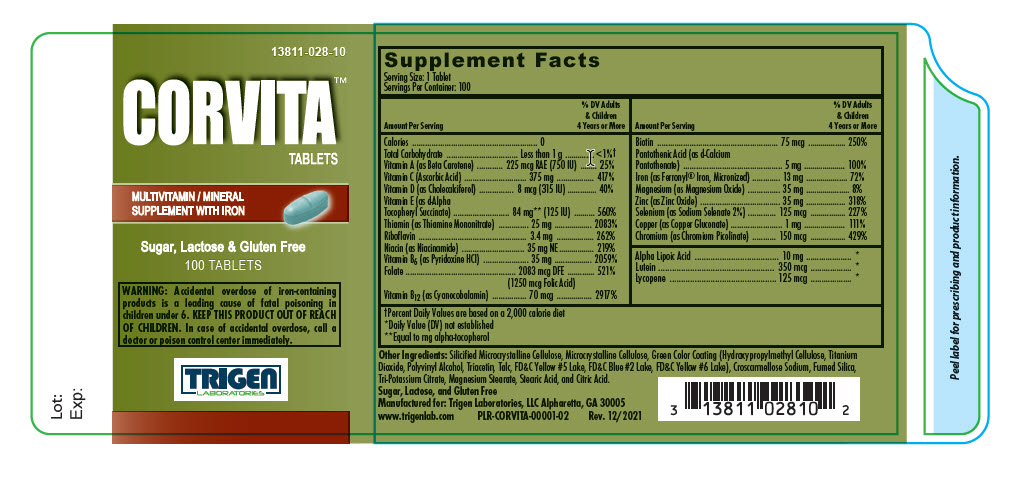 DRUG LABEL: Corvita
NDC: 13811-028 | Form: TABLET, COATED
Manufacturer: Trigen Laboratories, LLC
Category: other | Type: DIETARY SUPPLEMENT
Date: 20211220

ACTIVE INGREDIENTS: BETA CAROTENE 750 [iU]/1 1; .ALPHA.-TOCOPHEROL SUCCINATE, D- 125 [iU]/1 1; cholecalciferol 315 [iU]/1 1; ascorbic acid 375 mg/1 1; thiamine mononitrate 25 mg/1 1; riboflavin 3.4 mg/1 1; niacinamide 35 mg/1 1; folic acid 1.25 mg/1 1; pyridoxine Hydrochloride 35 mg/1 1; Biotin 75 ug/1 1; Pantothenic Acid 5 mg/1 1; cyanocobalamin 70 ug/1 1; Magnesium oxide 35 mg/1 1; Zinc oxide 35 mg/1 1; SODIUM SELENATE 125 ug/1 1; Chromium picolinate 150 ug/1 1; Copper gluconate 1 mg/1 1; IRON 13 mg/1 1; Lutein 350 ug/1 1; Lycopene 125 ug/1 1; THIOCTIC ACID 10 mg/1 1
INACTIVE INGREDIENTS: Cellulose, Microcrystalline; croscarmellose sodium; titanium dioxide; potassium citrate anhydrous; stearic acid; magnesium stearate; citric acid monohydrate; talc; FD&C Yellow No. 5; HYDROXYPROPYL CELLULOSE (1600000 WAMW); FD&C BLUE NO. 2--ALUMINUM LAKE; FD&C YELLOW NO. 6; TRIACETIN; SILICON DIOXIDE

CORVITA™
Multivitamin & Mineral
Supplement with Iron

SUPPLEMENT FACTS

Other Ingredients: Silicified Microcrystalline Cellulose, Microcrystalline Cellulose, Green Color Coating (Hydroxypropylmethyl Cellulose, Titanium Dioxide, Polyvinyl Alcohol, Triacetin, Talc, FD&C Yellow #5 Lake, FD&C Blue #2 Lake, FD&C Yellow #6 Lake), Croscarmellose Sodium, Fumed Silica, Tri- Potassium Citrate, Magnesium Stearate, Stearic Acid, and Citric Acid.

Sugar, Lactose, and Gluten Free

CORVITA™ is a prescribed Multivitamin/Mineral Supplement with Iron that is specially formulated and indicated for the distinct nutritional requirements of individuals with vitamin deficiencies.

INDICATIONS AND USAGE

CORVITA™ Multivitamins/Minerals with Iron tablets are indicated for the distinctive nutritional requirements of persons being treated for vitamin deficiencies by a physician.

CONTRAINDICATIONS

CORVITA™ Multivitamin/Mineral Supplement with Iron tablets should not be used by patients with known history of hypersensitivity to any of the listed ingredients or as directed by your physician.

WARNING

WARNING: Accidental overdose of iron-containing products is a leading cause of fatal poisoning in children under 6. KEEP THIS PRODUCT OUT OF REACH OF CHILDREN. In case of accidental overdose, call a doctor or poison control center immediately.

PRECAUTIONS

Folic acid alone is improper therapy in the treatment of pernicious anemia and other megaloblastic anemias where Vitamin B12 is deficient. Folic acid in doses above 0.1 mg daily, may obscure pernicious anemia assessment, such that hematologic remission can occur while neurological manifestations remain progressive.

This product contains FD&C Yellow No. 5 (tartrazine) which may cause allergic-type reactions (including bronchial asthma) in certain susceptible persons. Although the overall incidence of FD&C Yellow No. 5 (tartrazine) sensitivity in the general population is low, it is frequently seen in patients who also have aspirin hypersensitivity.

Biotin levels higher than the recommended daily allowance may cause interference with some laboratory tests, including cardiovascular diagnostic test (e.g. troponin) and hormone tests, and may lead to incorrect test results. Tell your healthcare provider about all prescription and over-the-counter medicines, vitamins, and dietary supplements that you take, including biotin.

DRUG INTERACTIONS

CORVITA™ Multivitamin & Mineral Supplement with Iron tablets are not recommended for and should not be given to patients receiving levodopa because the action of levodopa is antagonized by pyridoxine. There is a possibility of increased bleeding due to pyridoxine interaction with anticoagulants (e.g., Aspirin, Heparin, Clopidogrel).

ADVERSE REACTIONS

Adverse reactions have been reported with specific vitamins and minerals but generally at levels substantially higher than those contained in CORVITA™. However, allergic and idiosyncratic reactions are possible at lower levels. Iron, even at the usual recommended levels has been associated with gastrointestinal intolerance in some patients.

DESCRIPTION

CORVITA™ is a green coated, oval shaped tablet debossed with “VP 011”on one side, bisect on the other side.

DIRECTIONS FOR USE

Usual adult dosage is one bisected tablet daily, or as prescribed by a physician.

HOW SUPPLIED

Corvita™ tablets are supplied in bottles of 100 tablets.

Product Code: 13811-028-10

STORAGE

Store at 20°-25°C (68°-77°F), excursion permitted to 15°-30°C (59°-86°F) [See USP Controlled Room Temperature]. Protect from light and moisture and avoid excessive heat. Dispense in a tight, light resistant container as defined by the USP with a child-resistant closure.

KEEP OUT OF REACH OF CHILDREN.

For use on the order of a healthcare practitioner.

Call your doctor about side effects. To report side effects, call Trigen Laboratories, LLC at 1-770-509-4500 or FDA at 1-800-FDA-1088 or www.fda.gov/medwatch.

PLR-CORVITA-00001-02 Rev. 12/2021

Manufactured for:
Trigen Laboratories, LLC
Alpharetta, GA 30005

1-770-509-4500

PRINCIPAL DISPLAY PANEL - 100 Tablet Bottle Label

13811-028-10

CORVITA™ TABLETS

MULTIVITAMIN / MINERAL SUPPLEMENT WITH IRON

Sugar, Lactose and Gluten Free

100 TABLETS